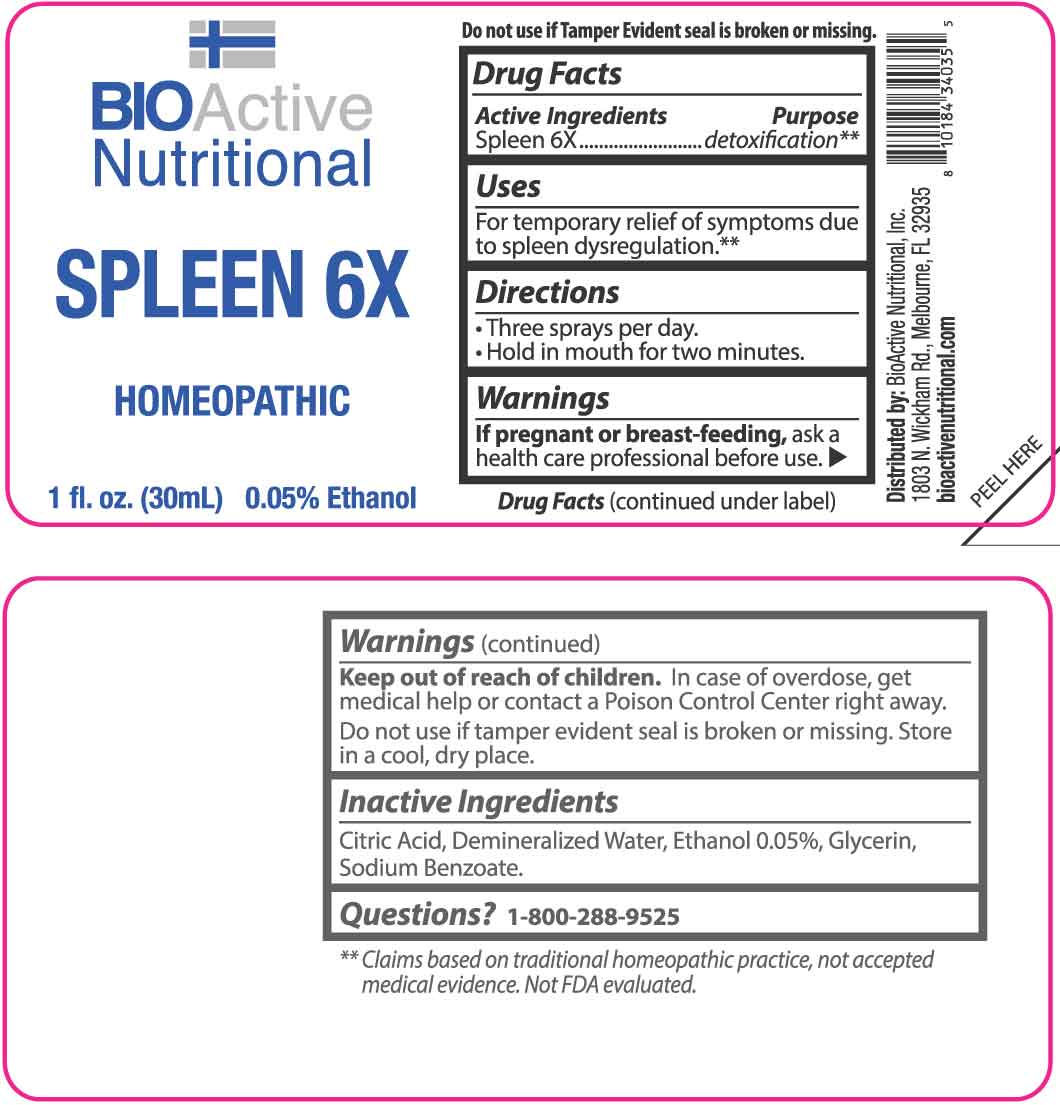 DRUG LABEL: Spleen
NDC: 43857-0119 | Form: LIQUID
Manufacturer: BioActive Nutritional, Inc.
Category: homeopathic | Type: HUMAN OTC DRUG LABEL
Date: 20251215

ACTIVE INGREDIENTS: BOS TAURUS SPLEEN 6 [hp_X]/1 mL
INACTIVE INGREDIENTS: WATER; GLYCERIN; SODIUM BENZOATE; CITRIC ACID MONOHYDRATE

DRUG FACTS:

ACTIVE INGREDIENTS:

Spleen 6X.

PURPOSE:

Spleen - detoxification**

**Claims based on traditional homeopathic practice, not accepted medical evidence. Not FDA evaluated.

USES:

For temporary relief of symptoms due to spleen dysregulation.**

**Claims based on traditional homeopathic practice, not accepted medical evidence. Not FDA evaluated.

WARNINGS:

If pregnant or breast-feeding, ask a health care professional before use.

Keep out of reach of children. In case of overdose, get medical help or contact a Poison Control Center right away.

Do not use if tamper evident seal is broken or missing. Store in a cool, dry place.

KEEP OUT OF REACH OF CHILDREN:

In case of overdose, get medical help or contact a Poison Control Center right away.

DIRECTIONS:

• Three sprays per day.

Hold in mouth for two minutes.

INACTIVE INGREDIENTS:

Citric Acid, Demineralized Water, Ethanol 0.05%, Glycerin, Sodium Benzoate.

QUESTIONS:

Distributed by:

BioActive Nutritional, Inc.

1803 N. Wickham Rd.

Melbourne, FL 32935

bioactivenutritional.com

1-800-288-9525

PACKAGE LABEL DISPLAY:

BIOActive Nutritional
SPLEEN 6X
HOMEOPATHIC
1 fl. oz. (30 mL)